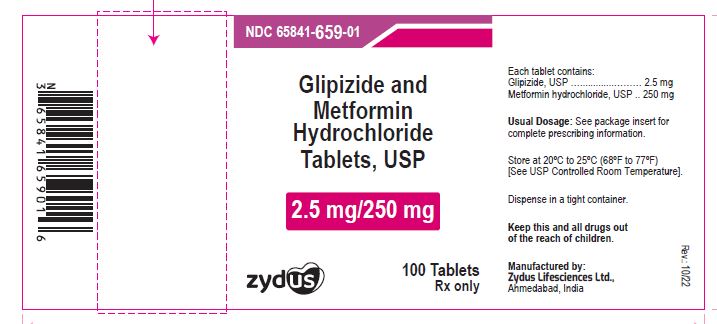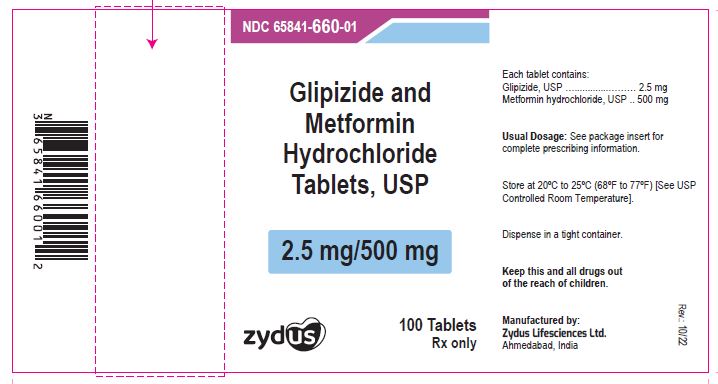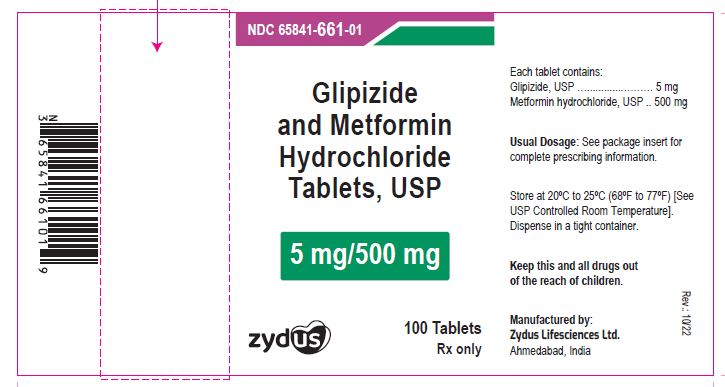 DRUG LABEL: Glipizide and Metformin  Hydrochloride
NDC: 65841-659 | Form: TABLET, FILM COATED
Manufacturer: Zydus Lifesciences Limited
Category: prescription | Type: HUMAN PRESCRIPTION DRUG LABEL
Date: 20241130

ACTIVE INGREDIENTS: GLIPIZIDE 2.5 mg/1 1; METFORMIN HYDROCHLORIDE 250 mg/1 1
INACTIVE INGREDIENTS: CROSCARMELLOSE SODIUM; HYPROMELLOSES; MAGNESIUM STEARATE; CELLULOSE, MICROCRYSTALLINE; POLYETHYLENE GLYCOL, UNSPECIFIED; POVIDONE; TITANIUM DIOXIDE; FERRIC OXIDE RED

Glipizide and Metformin Hydrochloride Tablets, USP

PACKAGE LABEL.PRINCIPAL DISPLAY PANEL

NDC 65841-659-01 in bottle of 100 tablets

Glipizide and Metformin Hydrochloride Tablets USP, 2.5 mg/250 mg

Rx only

100 tablets

NDC 65841-660-01 in bottle of 100 tablets

Glipizide and Metformin Hydrochloride Tablets USP, 2.5 mg/500 mg

Rx only

100 tablets

NDC 65841-661-01 in bottle of 100 tablets

Glipizide and Metformin Hydrochloride Tablets USP, 5 mg/500 mg

Rx only

100 tablets